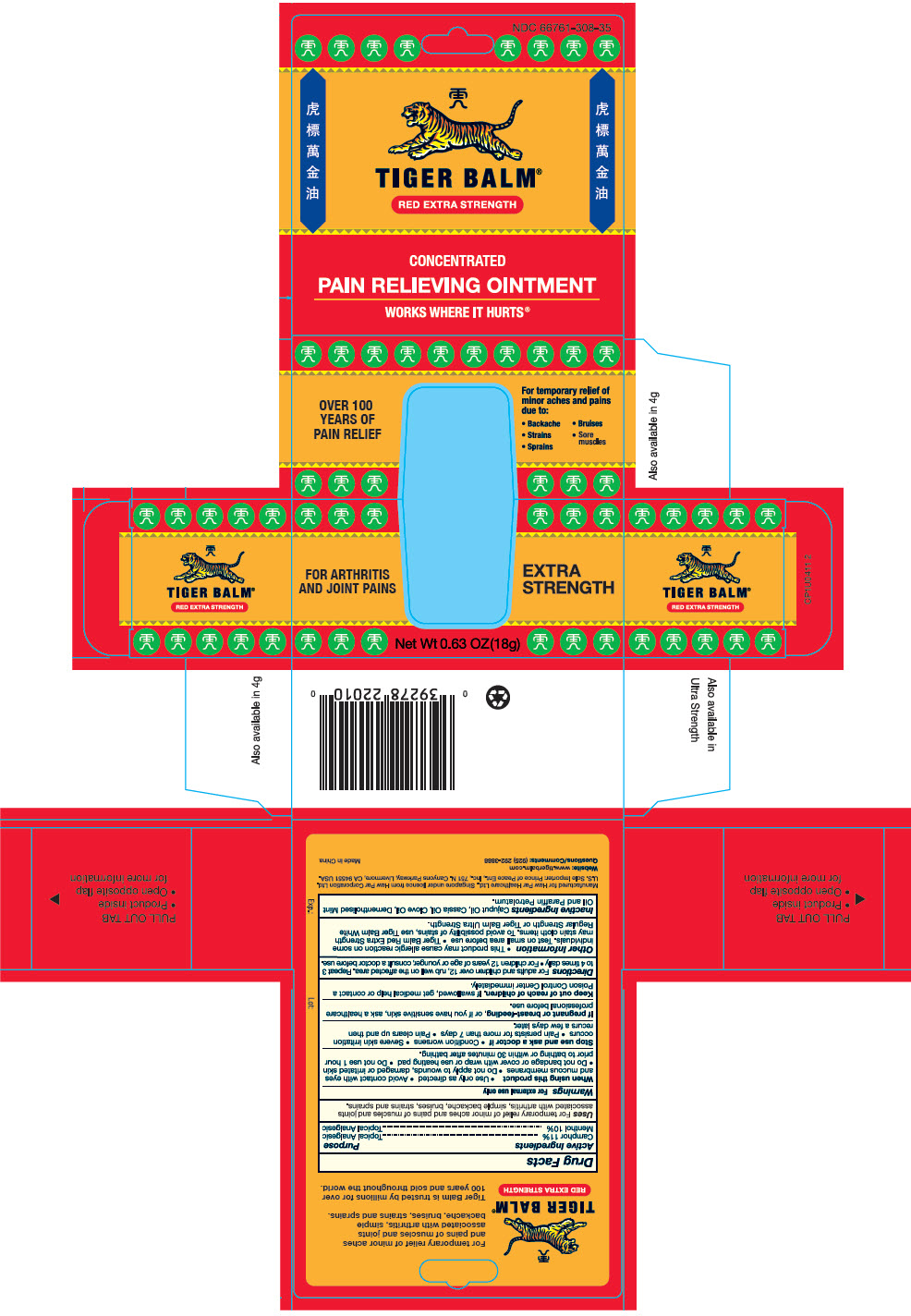 DRUG LABEL: Tiger Balm Red 
NDC: 66761-308 | Form: OINTMENT
Manufacturer: Haw Par Healthcare Ltd.
Category: otc | Type: HUMAN OTC DRUG LABEL
Date: 20251219

ACTIVE INGREDIENTS: Camphor (Synthetic) 110 mg/1 g; MENTHOL, UNSPECIFIED FORM 100 mg/1 g
INACTIVE INGREDIENTS: Cajuput Oil; Chinese Cinnamon Oil; Clove Oil

Tiger Balm®
Red Extra Strength

Drug Facts

ACTIVE INGREDIENT

Active Ingredients | Purpose
Camphor 11% | Topical Analgesic
Menthol 10% | Topical Analgesic

Uses

For temporary relief of minor aches and pains of muscles and joints associated with arthritis, simple backache, bruises, strains and sprains.

Warnings

For external use only

When using this product

- Use only as directed
- Avoid contact with eyes and mucous membranes
- Do not apply to wounds, damaged or irritated skin
- Do not bandage or cover with wrap or use heating pad

- Do not use 1 hour prior to bathing or 30 minutes after bathing.

Stop use and ask a doctor if

- Condition worsens
- Severe skin irritation occurs
- Pain persists for more than 7 days
- Pain clears up and then recurs a few days later.

PREGNANCY OR BREAST FEEDING

If pregnant or breast-feeding, or if you have sensitive skin, ask a healthcare professional before use.

Keep out of reach of children. If swallowed, get medical help or contact a Poison Control Center immediately.

Directions

- For adults and children over 12, rub well on the affected area. Repeat 3-4 times daily
- For children 12 years of age or younger, consult a doctor before use.

Other Information

- This product may cause allergic reaction in some individuals. Test on small area before use
- Tiger Balm Red Extra Strength may stain cloth items. To avoid possibility of strains, use Tiger Balm White Regular Strength or Tiger Balm Ultra Strength.

Inactive Ingredients

Cajuput Oil, Cassia Oil, Clove Oil, Dementholised Mint Oil and Paraffin Petrolatum.

Manufactured by Haw Par Healthcare Ltd., Singapore under licence
from Haw Par Corporation Ltd.

Questions

(510) 887-1899

PRINCIPAL DISPLAY PANEL - 18 g Jar Box

NDC 66761-308-35

TIGER BALM®
RED EXTRA STRENGTH

CONCENTRATED
PAIN RELIEVING OINTMENT
WORKS WHERE IT HURTS®

FOR ARTHRITIS
AND JOINT PAINS

EXTRA
STRENGTH

Net Wt 0.63 OZ(18g)